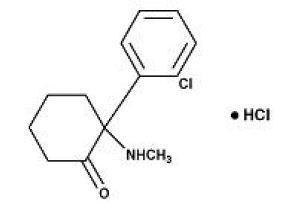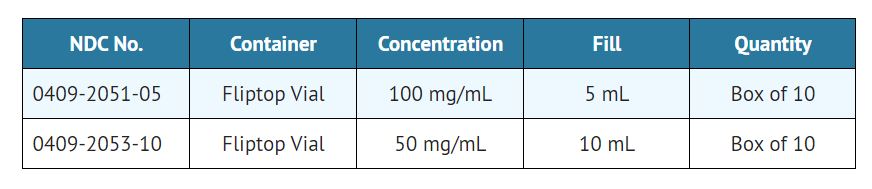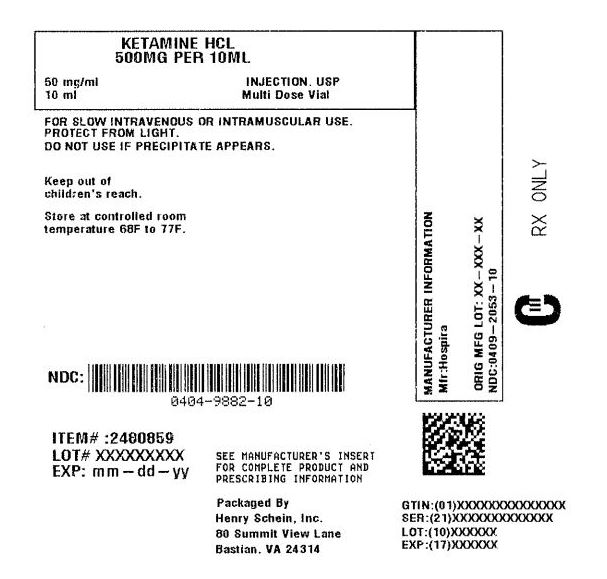 DRUG LABEL: KETAMINE HYDROCHLORIDE
NDC: 0404-9882 | Form: INJECTION, SOLUTION, CONCENTRATE
Manufacturer: Henry Schein, Inc.
Category: prescription | Type: HUMAN PRESCRIPTION DRUG LABEL
Date: 20251031
DEA Schedule: CIII

ACTIVE INGREDIENTS: KETAMINE HYDROCHLORIDE 50 mg/1 mL
INACTIVE INGREDIENTS: BENZETHONIUM CHLORIDE 0.1 mg/1 mL

Ketamine Hydrochloride Injection, USP
Rx only
CIII

SPECIAL NOTE

EMERGENCE REACTIONS HAVE OCCURRED IN APPROXIMATELY 12 PERCENT OF PATIENTS.

THE PSYCHOLOGICAL MANIFESTATIONS VARY IN SEVERITY BETWEEN PLEASANT DREAM-LIKE STATES, VIVID IMAGERY, HALLUCINATIONS, AND EMERGENCE DELIRIUM. IN SOME CASES THESE STATES HAVE BEEN ACCOMPANIED BY CONFUSION, EXCITEMENT, AND IRRATIONAL BEHAVIOR WHICH A FEW PATIENTS RECALL AS AN UNPLEASANT EXPERIENCE. THE DURATION ORDINARILY IS NO MORE THAN A FEW HOURS; IN A FEW CASES, HOWEVER, RECURRENCES HAVE TAKEN PLACE UP TO 24 HOURS POSTOPERATIVELY. NO RESIDUAL PSYCHOLOGICAL EFFECTS ARE KNOWN TO HAVE RESULTED FROM USE OF KETAMINE.

THE INCIDENCE OF THESE EMERGENCE PHENOMENA IS LEAST IN THE ELDERLY (OVER 65 YEARS OF AGE) PATIENT. ALSO, THEY ARE LESS FREQUENT WHEN THE DRUG IS GIVEN INTRAMUSCULARLY AND THE INCIDENCE IS REDUCED AS EXPERIENCE WITH THE DRUG IS GAINED.

THE INCIDENCE OF PSYCHOLOGICAL MANIFESTATIONS DURING EMERGENCE, PARTICULARLY DREAM-LIKE OBSERVATIONS AND EMERGENCE DELIRIUM, MAY BE REDUCED BY USING LOWER RECOMMENDED DOSAGES OF KETAMINE IN CONJUNCTION WITH INTRAVENOUS DIAZEPAM DURING INDUCTION AND MAINTENANCE OF ANESTHESIA. (See DOSAGE AND ADMINISTRATION Section). ALSO, THESE REACTIONS MAY BE REDUCED IF VERBAL, TACTILE, AND VISUAL STIMULATION OF THE PATIENT IS MINIMIZED DURING THE RECOVERY PERIOD. THIS DOES NOT PRECLUDE THE MONITORING OF VITAL SIGNS.

IN ORDER TO TERMINATE A SEVERE EMERGENCE REACTION, THE USE OF A SMALL HYPNOTIC DOSE OF A SHORT-ACTING OR ULTRA SHORT-ACTING BARBITURATE MAY BE REQUIRED.

WHEN KETAMINE IS USED ON AN OUTPATIENT BASIS, THE PATIENT SHOULD NOT BE RELEASED UNTIL RECOVERY FROM ANESTHESIA IS COMPLETE AND THEN SHOULD BE ACCOMPANIED BY A RESPONSIBLE ADULT.

DESCRIPTION

Ketamine hydrochloride is a nonbarbiturate general anesthetic chemically designated dl 2-(o-Chlorophenyl)-2-(methylamino) cyclohexanone hydrochloride. It is formulated as a slightly acid (pH 3.5–5.5) sterile solution for intravenous or intramuscular injection in concentrations containing the equivalent of either 50 or 100 mg ketamine base per milliliter and contains not more than 0.1 mg/mL benzethonium chloride added as a preservative. Ketamine hydrochloride has a molecular formula of C13H16ClNO ∙ HCl, a molecular weight of 274.19 and the following structural formula:

INDICATIONS AND USAGE

Ketamine hydrochloride injection is indicated as the sole anesthetic agent for diagnostic and surgical procedures that do not require skeletal muscle relaxation. Ketamine hydrochloride injection is best suited for short procedures but it can be used, with additional doses, for longer procedures.

Ketamine hydrochloride injection is indicated for the induction of anesthesia prior to the administration of other general anesthetic agents.

Ketamine hydrochloride injection is indicated to supplement low-potency agents, such as nitrous oxide.

Specific areas of application are described in the CLINICAL PHARMACOLOGY Section.

CLINICAL PHARMACOLOGY

Ketamine is a rapid-acting general anesthetic producing an anesthetic state characterized by profound analgesia, normal pharyngeal-laryngeal reflexes, normal or slightly enhanced skeletal muscle tone, cardiovascular and respiratory stimulation, and occasionally a transient and minimal respiratory depression. The mechanism of action is primarily due to antagonism of N-methyl-D-aspartate (NMDA receptors) in the central nervous system (CNS).

A patent airway is maintained partly by virtue of unimpaired pharyngeal and laryngeal reflexes. (See WARNINGS and PRECAUTIONS Sections.)

The biotransformation of ketamine includes N-dealkylation (metabolite I), hydroxylation of the cyclohexone ring (metabolites III and IV), conjugation with glucuronic acid and dehydration of the hydroxylated metabolites to form the cyclohexene derivative (metabolite II).

Following intravenous administration, the ketamine concentration has an initial slope (alpha phase) lasting about 45 minutes with a half-life of 10 to 15 minutes. This first phase corresponds clinically to the anesthetic effect of the drug. The anesthetic action is terminated by a combination of redistribution from the CNS to slower equilibrating peripheral tissues and by hepatic biotransformation to metabolite I. This metabolite is about 1/3 as active as ketamine in reducing halothane requirements (MAC) of the rat. The later half-life of ketamine (beta phase) is 2.5 hours.

The anesthetic state produced by ketamine has been termed "dissociative anesthesia" in that it appears to selectively interrupt association pathways of the brain before producing somatesthetic sensory blockade. It may selectively depress the thalamoneocortical system before significantly obtunding the more ancient cerebral centers and pathways (reticular-activating and limbic systems).

Elevation of blood pressure begins shortly after injection, reaches a maximum within a few minutes and usually returns to preanesthetic values within 15 minutes after injection. In the majority of cases, the systolic and diastolic blood pressure peaks from 10% to 50% above preanesthetic levels shortly after induction of anesthesia, but the elevation can be higher or longer in individual cases (see CONTRAINDICATIONS Section).

Ketamine has a wide margin of safety; several instances of unintentional administration of overdoses of ketamine (up to ten times that usually required) have been followed by prolonged but complete recovery.

Ketamine has been studied in over 12,000 operative and diagnostic procedures, involving over 10,000 patients from 105 separate studies. During the course of these studies ketamine hydrochloride was administered as the sole agent, as induction for other general agents, or to supplement low-potency agents.

Specific areas of application have included the following:

1. debridement, painful dressings, and skin grafting in burn patients, as well as other superficial surgical procedures.
2. neurodiagnostic procedures such as pneumonencephalograms, ventriculograms, myelograms, and lumbar punctures. See also Precaution concerning increased intracranial pressure.
3. diagnostic and operative procedures of the eye, ear, nose, and mouth, including dental extractions.
4. diagnostic and operative procedures of the pharynx, larynx, or bronchial tree. NOTE: Muscle relaxants, with proper attention to respiration, may be required (see PRECAUTIONS Section).
5. sigmoidoscopy and minor surgery of the anus and rectum, and circumcision.
6. extraperitoneal procedures used in gynecology such as dilatation and curettage.
7. orthopedic procedures such as closed reductions, manipulations, femoral pinning, amputations, and biopsies.
8. as an anesthetic in poor-risk patients with depression of vital functions.
9. in procedures where the intramuscular route of administration is preferred.
10. in cardiac catheterization procedures.

In these studies, the anesthesia was rated either "excellent" or "good" by the anesthesiologist and the surgeon at 90% and 93%, respectively; rated "fair" at 6% and 4%, respectively; and rated "poor" at 4% and 3%, respectively. In a second method of evaluation, the anesthesia was rated "adequate" in at least 90%, and "inadequate" in 10% or less of the procedures.

CONTRAINDICATIONS

Ketamine hydrochloride is contraindicated in those in whom a significant elevation of blood pressure would constitute a serious hazard and in those who have shown hypersensitivity to the drug.

WARNINGS

Cardiac function should be continually monitored during the procedure in patients found to have hypertension or cardiac decompensation.

Postoperative confusional states may occur during the recovery period. (See SPECIAL NOTE).

Respiratory depression may occur with overdosage or too rapid a rate of administration of ketamine, in which case supportive ventilation should be employed. Mechanical support of respiration is preferred to administration of analeptics.

Pediatric Neurotoxicity

Published animal studies demonstrate that the administration of anesthetic and sedation drugs that block NMDA receptors and/or potentiate GABA activity increase neuronal apoptosis in the developing brain and result in long-term cognitive deficits when used for longer than 3 hours. The clinical significance of these findings is not clear. However, based on the available data, the window of vulnerability to these changes is believed to correlate with exposures in the third trimester of gestation through the first several months of life, but may extend out to approximately three years of age in humans. (See PRECAUTIONS/Pregnancy).

Some published studies in children suggest that similar deficits may occur after repeated or prolonged exposures to anesthetic agents early in life and may result in adverse cognitive or behavioral effects. These studies have substantial limitations, and it is not clear if the observed effects are due to the anesthetic/sedation drug administration or other factors such as the surgery or underlying illness.

Anesthetic and sedation drugs are a necessary part of the care of children needing surgery, other procedures, or tests that cannot be delayed, and no specific medications have been shown to be safer than any other. Decisions regarding the timing of any elective procedures requiring anesthesia should take into consideration the benefits of the procedure weighed against the potential risks.

PRECAUTIONS

General

Ketamine should be used by or under the direction of physicians experienced in administering general anesthetics and in maintenance of an airway and in the control of respiration.

Because pharyngeal and laryngeal reflexes are usually active, ketamine should not be used alone in surgery or diagnostic procedures of the pharynx, larynx, or bronchial tree. Mechanical stimulation of the pharynx should be avoided, whenever possible, if ketamine is used alone. Muscle relaxants, with proper attention to respiration, may be required in both of these instances.

Resuscitative equipment should be ready for use.

The incidence of emergence reactions may be reduced if verbal and tactile stimulation of the patient is minimized during the recovery period. This does not preclude the monitoring of vital signs (see SPECIAL NOTE).

The intravenous dose should be administered over a period of 60 seconds. More rapid administration may result in respiratory depression or apnea and enhanced pressor response.

In surgical procedures involving visceral pain pathways, ketamine should be supplemented with an agent which obtunds visceral pain.

Use with caution in the chronic alcoholic and the acutely alcohol-intoxicated patient.

An increase in cerebrospinal fluid pressure has been reported following administration of ketamine hydrochloride. Use with extreme caution in patients with preanesthetic elevated cerebrospinal fluid pressure.

Carcinogenesis, Mutagenesis, Impairment of Fertility

Carcinogenesis

Long-term animal studies have not been conducted to evaluate the carcinogenic potential of ketamine.

Mutagenesis

In a published report, ketamine was clastogenic in the in vitro chromosomal aberration assay.

Impairment of Fertility

Adequate studies to evaluate the impact of ketamine on male or female fertility have not been conducted. Male and female rats were treated intravenously with 10 mg/kg ketamine (0.8 times the average human intravenous induction dose of 2 mg/kg based on body surface area) on Days 11, 10, and 9 prior to mating. No impact on fertility was noted; however, this study design does not adequately characterize the impact of a drug on fertility endpoints.

Pregnancy

Risk Summary

There are no adequate and well-controlled studies of ketamine in pregnant women. In animal reproduction studies in rats developmental delays (hypoplasia of skeletal tissues) were noted at 0.3 times the human intramuscular dose of 10 mg/kg. In rabbits, developmental delays and increased fetal resorptions were noted at 0.6 times the human dose. Published studies in pregnant primates demonstrate that the administration of anesthetic and sedation drugs that block NMDA receptors and/or potentiate GABA activity during the period of peak brain development increases neuronal apoptosis in the developing brain of the offspring when used for longer than 3 hours. There are no data on pregnancy exposures in primates corresponding to periods prior to the third trimester in humans.

The estimated background risk of major birth defects and miscarriage for the indicated population is unknown. All pregnancies have a background risk of birth defect, loss, or other adverse outcomes. In the U.S. general population, the estimated background risk of major birth defects and miscarriage in clinically recognized pregnancies is 2–4% and 15–20%, respectively.

Clinical Considerations

Since the safe use in pregnancy, including obstetrics (either vaginal or abdominal delivery), has not been established, such use is not recommended (see ANIMAL PHARMACOLOGY AND TOXICOLOGY).

Data

Animal Data

Pregnant rats were treated intramuscularly with 20 mg/kg ketamine (0.3 times the human intramuscular dose of 10 mg/kg based on body surface area) on either Gestation Days 6 to 10 or Gestation Days 11 to 15. Ketamine treatment produced an increased incidence of hypoplastic skull, phalanges, and sternebrae in the pups.

Pregnant rabbits were treated intramuscularly with 20 mg/kg ketamine (0.6 times the human intramuscular dose of 10 mg/kg based on body surface area) on either Gestation Days 6 to 10 or Gestation Days 11 to 15. An increase in resorptions and skeletal hypoplasia of the fetuses were noted. Additional pregnant rabbits were treated intramuscularly with a single dose 60 mg/kg (1.9 times the human intramuscular dose of 10 mg/kg based on body surface area) on Gestation Day 6 only. Skeletal hypoplasia was reported in the fetuses.

In a study where pregnant rats were treated intramuscularly with 20 mg/kg ketamine (0.3 times the human intramuscular dose of 10 mg/kg based on body surface area) from Gestation Day 18 to 21. There was a slight increase in incidence of delayed parturition by one day in treated dams of this group. No adverse effects on the litters or pups were noted; however, learning and memory assessments were not completed.

Three pregnant beagle dogs were treated intramuscularly with 25 mg/kg ketamine (1.3 times the human intramuscular dose of 10 mg/kg based on body surface area) twice weekly for the three weeks of the first, second, and third trimesters of pregnancy, respectively, without the development of adverse effects in the pups.

In a published study in primates, administration of an anesthetic dose of ketamine for 24 hours on Gestation Day 122 increased neuronal apoptosis in the developing brain of the fetus. In other published studies, administration of either isoflurane or propofol for 5 hours on Gestation Day 120 resulted in increased neuronal and oligodendrocyte apoptosis in the developing brain of the offspring. With respect to brain development, this time period corresponds to the third trimester of gestation in the human. The clinical significance of these findings is not clear; however, studies in juvenile animals suggest neuroapoptosis correlates with long-term cognitive deficits. (See WARNINGS/Pediatric Neurotoxicity, Pediatric Use, and ANIMAL TOXICOLOGY AND PHARMACOLOGY).

Information for Patients

Risk of Drowsiness

As appropriate, especially in cases where early discharge is possible, the duration of ketamine and other drugs employed during the conduct of anesthesia should be considered. The patients should be cautioned that driving an automobile, operating hazardous machinery or engaging in hazardous activities should not be undertaken for 24 hours or more (depending upon the dosage of ketamine and consideration of other drugs employed) after anesthesia.

Effect of anesthetic and sedation drugs on early brain development

Studies conducted in young animals and children suggest repeated or prolonged use of general anesthetic or sedation drugs in children younger than 3 years may have negative effects on their developing brains. Discuss with parents and caregivers the benefits, risks, and timing and duration of surgery or procedures requiring anesthetic and sedation drugs (See WARNINGS/Pediatric Neurotoxicity).

Drug Interactions

Prolonged recovery time may occur if barbiturates and/or narcotics are used concurrently with ketamine.

Ketamine is clinically compatible with the commonly used general and local anesthetic agents when an adequate respiratory exchange is maintained.

Geriatric Use

Clinical studies of ketamine hydrochloride did not include sufficient numbers of subjects aged 65 and over to determine whether they respond differently from younger subjects. Other reported clinical experience has not identified differences in responses between the elderly and younger patients. In general, dose selection for an elderly patient should be cautious, usually starting at the low end of the dosing range, reflecting the greater frequency of decreased hepatic, renal, or cardiac function, and of concomitant disease or other drug therapy.

Pediatric Use

Safety and effectiveness in pediatric patients below the age of 16 have not been established.

Published juvenile animal studies demonstrate that the administration of anesthetic and sedation drugs, such as ketamine, that either block NMDA receptors or potentiate the activity of GABA during the period of rapid brain growth or synaptogenesis, results in widespread neuronal and oligodendrocyte cell loss in the developing brain and alterations in synaptic morphology and neurogenesis. Based on comparisons across species, the window of vulnerability to these changes is believed to correlate with exposures in the third trimester of gestation through the first several months of life, but may extend out to approximately 3 years of age in humans.

In primates, exposure to 3 hours of ketamine that produced a light surgical plane of anesthesia did not increase neuronal cell loss, however, treatment regimens of 5 hours or longer of isoflurane increased neuronal cell loss. Data from isoflurane-treated rodents and ketamine-treated primates suggest that the neuronal and oligodendrocyte cell losses are associated with prolonged cognitive deficits in learning and memory. The clinical significance of these nonclinical findings is not known, and healthcare providers should balance the benefits of appropriate anesthesia in pregnant women, neonates, and young children who require procedures with the potential risks suggested by the nonclinical data. (See WARNINGS/Pediatric Neurotoxicity, Pregnancy).

ADVERSE REACTIONS

Cardiovascular: Blood pressure and pulse rate are frequently elevated following administration of ketamine alone. However, hypotension and bradycardia have been observed. Arrhythmia has also occurred.

Respiration: Although respiration is frequently stimulated, severe depression of respiration or apnea may occur following rapid intravenous administration of high doses of ketamine. Laryngospasms and other forms of airway obstruction have occurred during ketamine anesthesia.

Eye: Diplopia and nystagmus have been noted following ketamine administration. It also may cause a slight elevation in intraocular pressure measurement.

Genitourinary: In individuals with history of chronic ketamine use or abuse, lower urinary tract and bladder symptoms including dysuria, increased urinary frequency, urgency, urge incontinence, and hematuria have been reported (see DOSAGE AND ADMINISTRATION Section). In addition, diagnostic studies performed to assess the cause of these symptoms have reported cystitis (including cystitis non-infective, cystitis interstitial, cystitis ulcerative, cystitis erosive and cystitis hemorrhagic) as well as hydronephrosis and reduced bladder capacity.

Psychological: (See SPECIAL NOTE).

Neurological: In some patients, enhanced skeletal muscle tone may be manifested by tonic and clonic movements sometimes resembling seizures (see DOSAGE AND ADMINISTRATION Section).

Gastrointestinal: Anorexia, nausea and vomiting have been observed; however, this is not usually severe and allows the great majority of patients to take liquids by mouth shortly after regaining consciousness (see DOSAGE AND ADMINISTRATION Section).

General: Anaphylaxis. Local pain and exanthema at the injection site have infrequently been reported. Transient erythema and/or morbilliform rash have also been reported.

For medical advice about adverse reactions contact your medical professional. To report SUSPECTED ADVERSE REACTIONS, contact Hospira, Inc. at 1-800-441-4100 or FDA at 1-800-FDA-1088 or www.fda.gov/medwatch.

DRUG ABUSE AND DEPENDENCE

Ketamine has been reported being used as a drug of abuse.

Reports suggest that ketamine produces a variety of symptoms including, but not limited to anxiety, dysphoria, disorientation, insomnia, flashbacks, hallucinations, and psychotic episodes.

Ketamine dependence and tolerance are possible following prolonged administration. A withdrawal syndrome with psychotic features has been described following discontinuation of long-term ketamine use. Therefore, ketamine should be prescribed and administered with caution.

OVERDOSAGE

Respiratory depression may occur with overdosage or too rapid a rate of administration of ketamine, in which case supportive ventilation should be employed. Mechanical support of respiration is preferred to administration of analeptics.

DOSAGE AND ADMINISTRATION

Parenteral drug products should be inspected visually for particulate matter and discoloration prior to administration, whenever solution and container permit.

Note: Barbiturates and ketamine, being chemically incompatible because of precipitate formation, should not be injected from the same syringe.

If the ketamine dose is augmented with diazepam, the two drugs must be given separately. Do not mix ketamine hydrochloride and diazepam in syringe or infusion flask. For additional information on the use of diazepam, refer to the WARNINGS and DOSAGE AND ADMINISTRATION Sections of the diazepam insert.

Preoperative Preparations

1. While vomiting has been reported following ketamine administration, some airway protection may be afforded because of active laryngeal-pharyngeal reflexes. However, since aspiration may occur with ketamine and since protective reflexes may also be diminished by supplementary anesthetics and muscle relaxants, the possibility of aspiration must be considered. Ketamine is recommended for use in the patient whose stomach is not empty when, in the judgment of the practitioner, the benefits of the drug outweigh the possible risks.
2. Atropine, scopolamine, or another drying agent should be given at an appropriate interval prior to induction.
Onset and Duration

Because of rapid induction following the initial intravenous injection, the patient should be in a supported position during administration.

The onset of action of ketamine is rapid; an intravenous dose of 2 mg/kg of body weight usually produces surgical anesthesia within 30 seconds after injection, with the anesthetic effect usually lasting five to ten minutes. If a longer effect is desired, additional increments can be administered intravenously or intramuscularly to maintain anesthesia without producing significant cumulative effects.

Intramuscular doses, in a range of 9 to 13 mg/kg usually produce surgical anesthesia within 3 to 4 minutes following injection, with the anesthetic effect usually lasting 12 to 25 minutes.

Dosage

As with other general anesthetic agents, the individual response to ketamine is somewhat varied depending on the dose, route of administration, and age of patient, so that dosage recommendation cannot be absolutely fixed. The drug should be titrated against the patient's requirements.

In individuals with a history of chronic ketamine use for off-label indications, there have been case reports of genitourinary pain that may be related to the ketamine treatment, not the underlying condition (see ADVERSE REACTIONS Section). Consider cessation of ketamine if genitourinary pain continues in the setting of other genitourinary symptoms.

Induction

Intravenous Route

The initial dose of ketamine administered intravenously may range from 1 mg/kg to 4.5 mg/kg. The average amount required to produce five to ten minutes of surgical anesthesia has been 2 mg/kg.

Alternatively, in adult patients an induction dose of 1 mg to 2 mg/kg intravenous ketamine at a rate of 0.5 mg/kg/min may be used for induction of anesthesia. In addition, diazepam in 2 mg to 5 mg doses, administered in a separate syringe over 60 seconds, may be used. In most cases, 15 mg of intravenous diazepam or less will suffice. The incidence of psychological manifestations during emergence, particularly dream-like observations and emergence delirium, may be reduced by this induction dosage program.

Note: The 100 mg/mL concentration of ketamine should not be injected intravenously without proper dilution. It is recommended the drug be diluted with an equal volume of either Sterile Water for Injection, USP, Normal Saline, or 5% Dextrose in Water.

Rate of Administration

It is recommended that ketamine be administered slowly (over a period of 60 seconds). More rapid administration may result in respiratory depression and enhanced pressor response.

Intramuscular Route

The initial dose of ketamine administered intramuscularly may range from 6.5 to 13 mg/kg. A dose of 10 mg/kg will usually produce 12 to 25 minutes of surgical anesthesia.

Maintenance of Anesthesia

The maintenance dose should be adjusted according to the patient's anesthetic needs and whether an additional anesthetic agent is employed.

Increments of one-half to the full induction dose may be repeated as needed for maintenance of anesthesia. However, it should be noted that purposeless and tonic-clonic movements of extremities may occur during the course of anesthesia. These movements do not imply a light plane and are not indicative of the need for additional doses of the anesthetic.

It should be recognized that the larger the total dose of ketamine administered, the longer will be the time to complete recovery.

Adult patients induced with ketamine augmented with intravenous diazepam may be maintained on ketamine given by slow microdrip infusion technique at a dose of 0.1 to 0.5 mg/minute, augmented with diazepam 2 to 5 mg administered intravenously as needed. In many cases 20 mg or less of intravenous diazepam total for combined induction and maintenance will suffice. However, slightly more diazepam may be required depending on the nature and duration of the operation, physical status of the patient, and other factors. The incidence of psychological manifestations during emergence, particularly dream-like observations and emergence delirium, may be reduced by this maintenance dosage program.

Dilution

To prepare a dilute solution containing 1 mg of ketamine per mL, aseptically transfer 10 mL from a 50 mg per mL vial or 5 mL from a 100 mg per mL vial to 500 mL of 5% Dextrose Injection, USP or Sodium Chloride (0.9%) Injection, USP (Normal Saline) and mix well. The resultant solution will contain 1 mg of ketamine per mL.

The fluid requirements of the patient and duration of anesthesia must be considered when selecting the appropriate dilution of ketamine hydrochloride injection. If fluid restriction is required, ketamine hydrochloride injection can be added to a 250 mL infusion as described above to provide a ketamine concentration of 2 mg/mL.

Supplementary Agents

Ketamine is clinically compatible with the commonly used general and local anesthetic agents when an adequate respiratory exchange is maintained.

The regimen of a reduced dose of ketamine supplemented with diazepam can be used to produce balanced anesthesia by combination with other agents such as nitrous oxide and oxygen.

HOW SUPPLIED

Ketamine Hydrochloride Injection, USP is supplied as the hydrochloride in concentrations equivalent to ketamine base.

Color of solution may vary from colorless to very slightly yellowish and may darken upon prolonged exposure to light. This darkening does not affect potency. Do not use if a precipitate appears.

Store between 20° to 25°C (68° to 77°F). (See USP Controlled Room Temperature.)

Protect from light.

Product repackaged by: Henry Schein, Inc., Bastian, VA 24314
From Original Manufacturer/Distributor's NDC and Unit of Sale | To Henry Schein Repackaged Product NDC and Unit of Sale | Total Strength/Total Volume (Concentration) per unit
NDC 0409-2051-05 Box of 10 5 mL Multiple-dose Fliptop Vial | NDC 0404-9881-05 1 5 mL Multiple-dose Fliptop vial in a bag (Vial bears NDC 0409-2051-15) | 500 mg/5 mL (100 mg/mL)
NDC 0409-2053-10 Box of 10 10 mL Multiple-dose Fliptop Vial | NDC 0404-9882-10 1 10 mL Multiple-dose Fliptop vial in a bag (Vial bears NDC 0409-2053-20) | 500 mg/10 mL (50 mg/mL)

ANIMAL PHARMACOLOGY AND TOXICOLOGY

Published studies in animals demonstrate that the use of anesthetic agents during the period of rapid brain growth or synaptogenesis results in widespread neuronal and oligodendrocyte cell loss in the developing brain and alterations in synaptic morphology and neurogenesis. Based on comparisons across species, the window of vulnerability to these changes is believed to correlate with exposures in the third trimester through the first several months of life, but may extend out to approximately 3 years of age in humans.

In primates, exposure to 3 hours of an anesthetic regimen that produced a light surgical plane of anesthesia did not increase neuronal cell loss, however, treatment regimens of 5 hours or longer increased neuronal cell loss. Data in rodents and in primates suggest that the neuronal and oligodendrocyte cell losses are associated with subtle but prolonged cognitive deficits in learning and memory. The clinical significance of these nonclinical findings is not known, and healthcare providers should balance the benefits of appropriate anesthesia in neonates and young children who require procedures against the potential risks suggested by the nonclinical data. (See WARNINGS/Pediatric Neurotoxicity, Use in Pregnancy, and Pediatric Use).

In published studies, intraperitoneal administration of ketamine at doses greater than 40 mg/kg induced vacuolation in neuronal cells of the posterior cingulate and retrosplenial cortices in adult rats, similar to what has been reported in rodents administered other NMDA receptor antagonists. These vacuoles were demonstrated to be reversible and did not progress to degeneration or neuronal death up to doses of 80 mg/kg (1.2 times the human dose of 10 mg/kg based on body surface area). A no-effect level for neuronal vacuolation was 20 mg/kg intraperitoneal (0.3 times a human dose of 10 mg/kg on a body surface area basis). The window of vulnerability to these changes is believed to correlate with exposures in humans from the onset of puberty through adulthood. The relevance of this finding to humans is unknown.

HOSPIRA, INC., LAKE FOREST, IL 60045 USA

LAB-1028-2.0

Revised: 9/2018